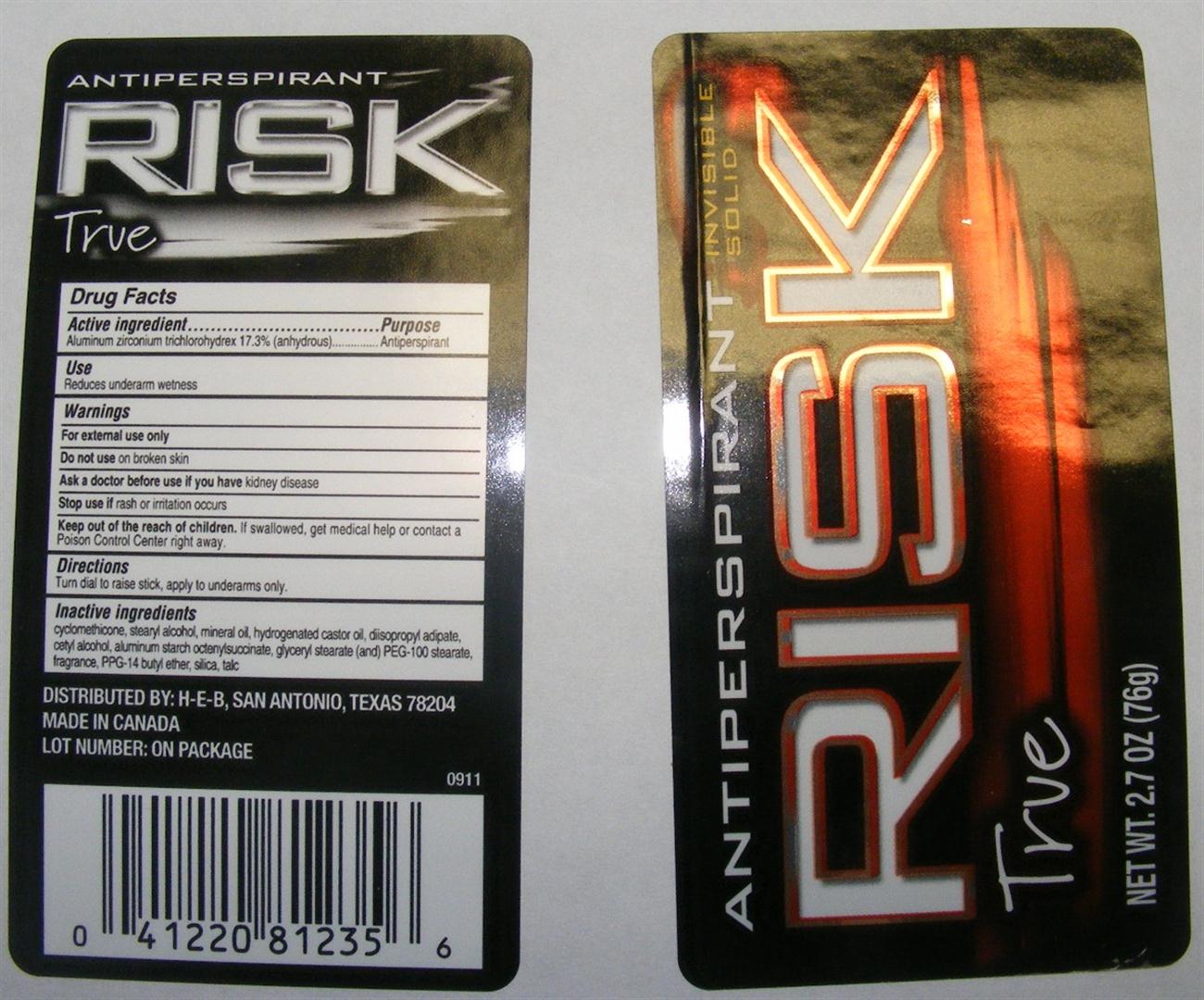 DRUG LABEL: Risk True 
NDC: 37808-689 | Form: STICK
Manufacturer: H-E-B
Category: otc | Type: HUMAN OTC DRUG LABEL
Date: 20110325

ACTIVE INGREDIENTS: Aluminum Zirconium Trichlorohydrex Gly 17.3 g/100 g
INACTIVE INGREDIENTS: CYCLOMETHICONE 5; STEARYL ALCOHOL; Mineral Oil; Hydrogenated Castor Oil; DIISOPROPYL ADIPATE; CETYL ALCOHOL; ALUMINUM STARCH OCTENYLSUCCINATE; GLYCERYL MONOSTEARATE; POLYOXYL 100 STEARATE; PPG-14 BUTYL ETHER; SILICON DIOXIDE; Talc

Risk True Invisible Solid Antiperspirant

Active Ingredient

Aluminum Zirconium Trichlorohydrex 17.3% (anhydrous)

Purpose

Antiperspirant

Use

Reduces underarm wetness

Warnings

For external use only

Do not use on broken skin

Ask a doctor before use if you have kidney disease

Stop use if rash or irritation occurs

Keep out of the reach of children. If swallowed, get medical help or contact a Poison Control Center right away.

Directions

Turn dial to raise stick, apply to underarms only.

Inactive ingredients
cyclomethicone, stearyl alcohol, mineral oil, hydrogenated castor oil, diisopropyl adipate, cetyl alcohol, aluminum starch octenylsuccinate, glyceryl stearate (and) PEG-100 stearate, fragrance, PPG-14 butyl ether, silica, talc

Image of 76 g Label